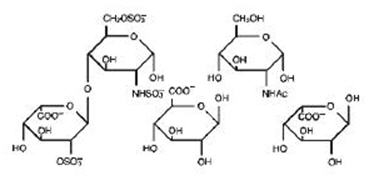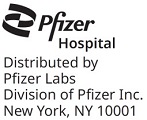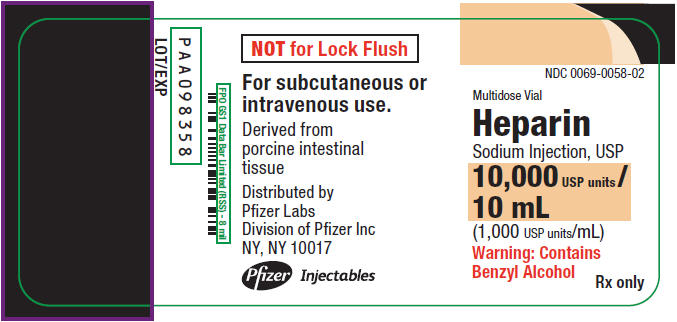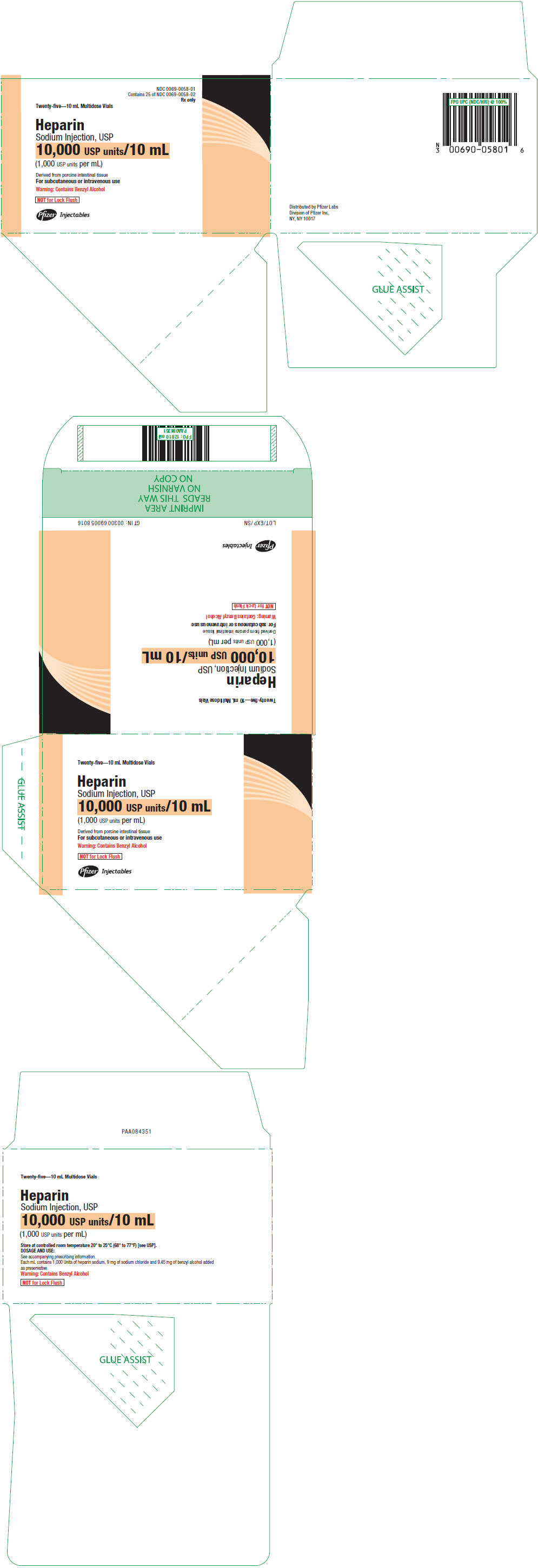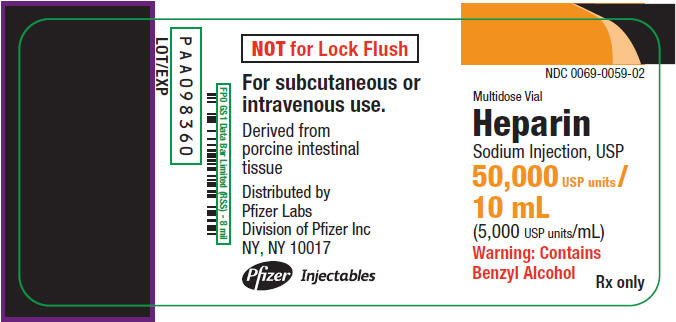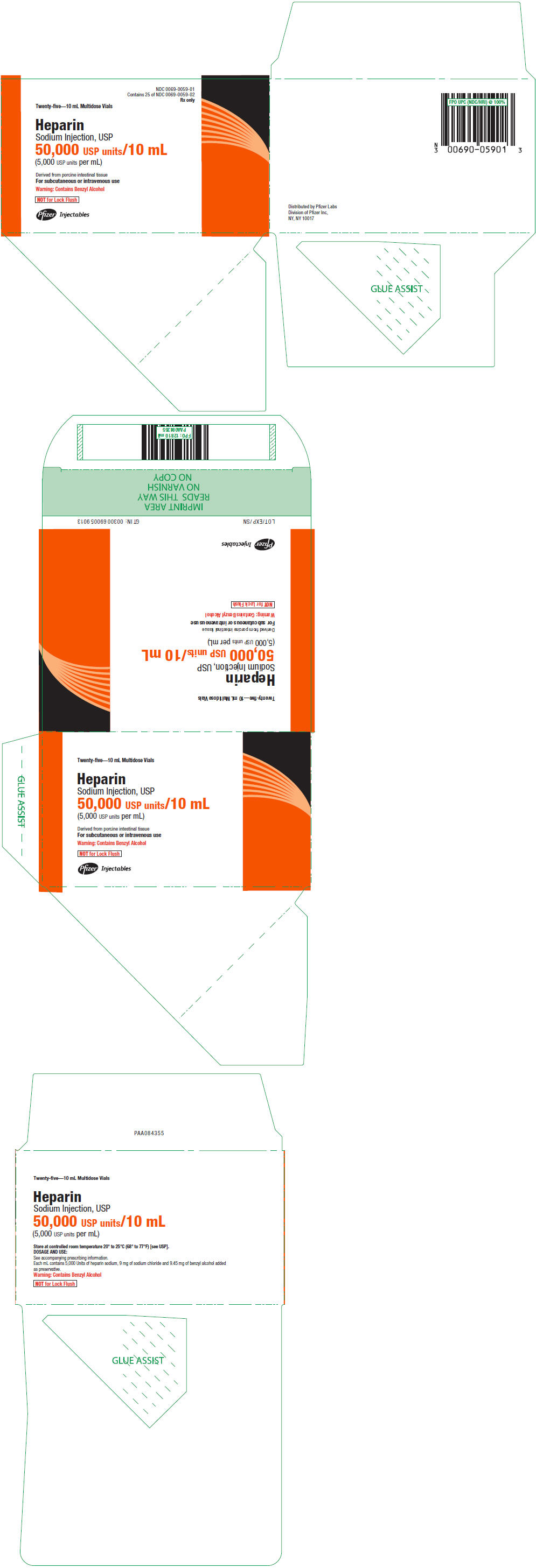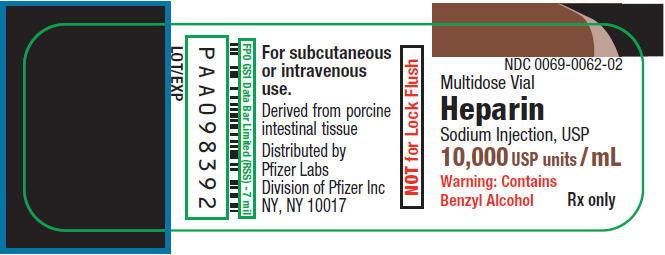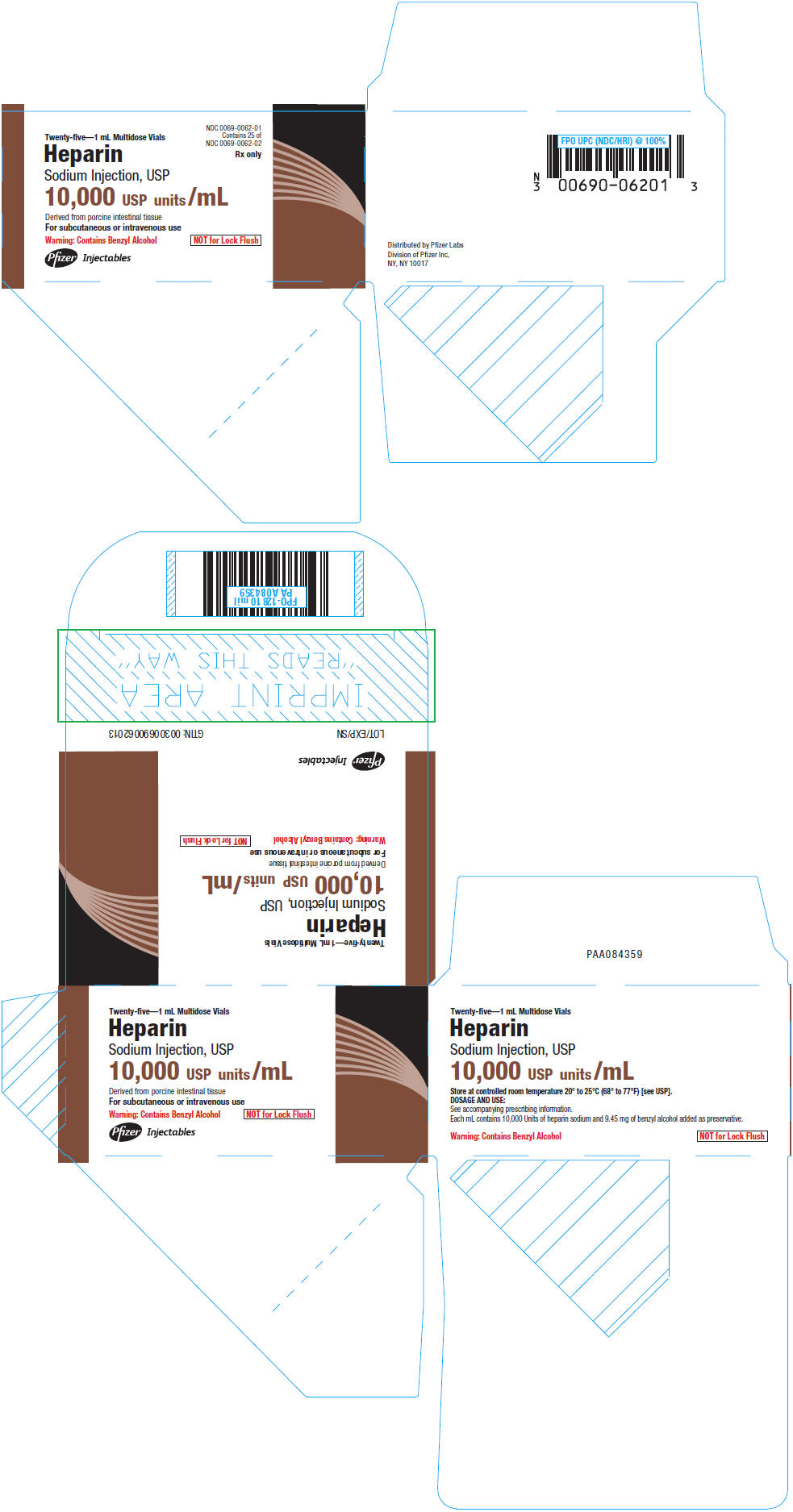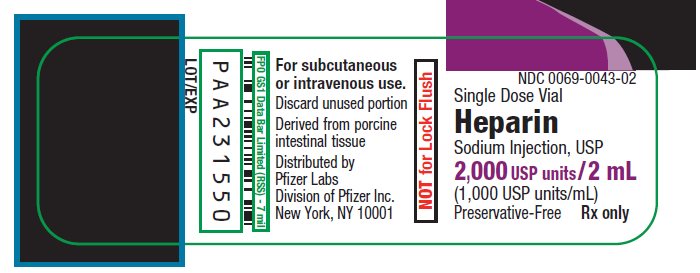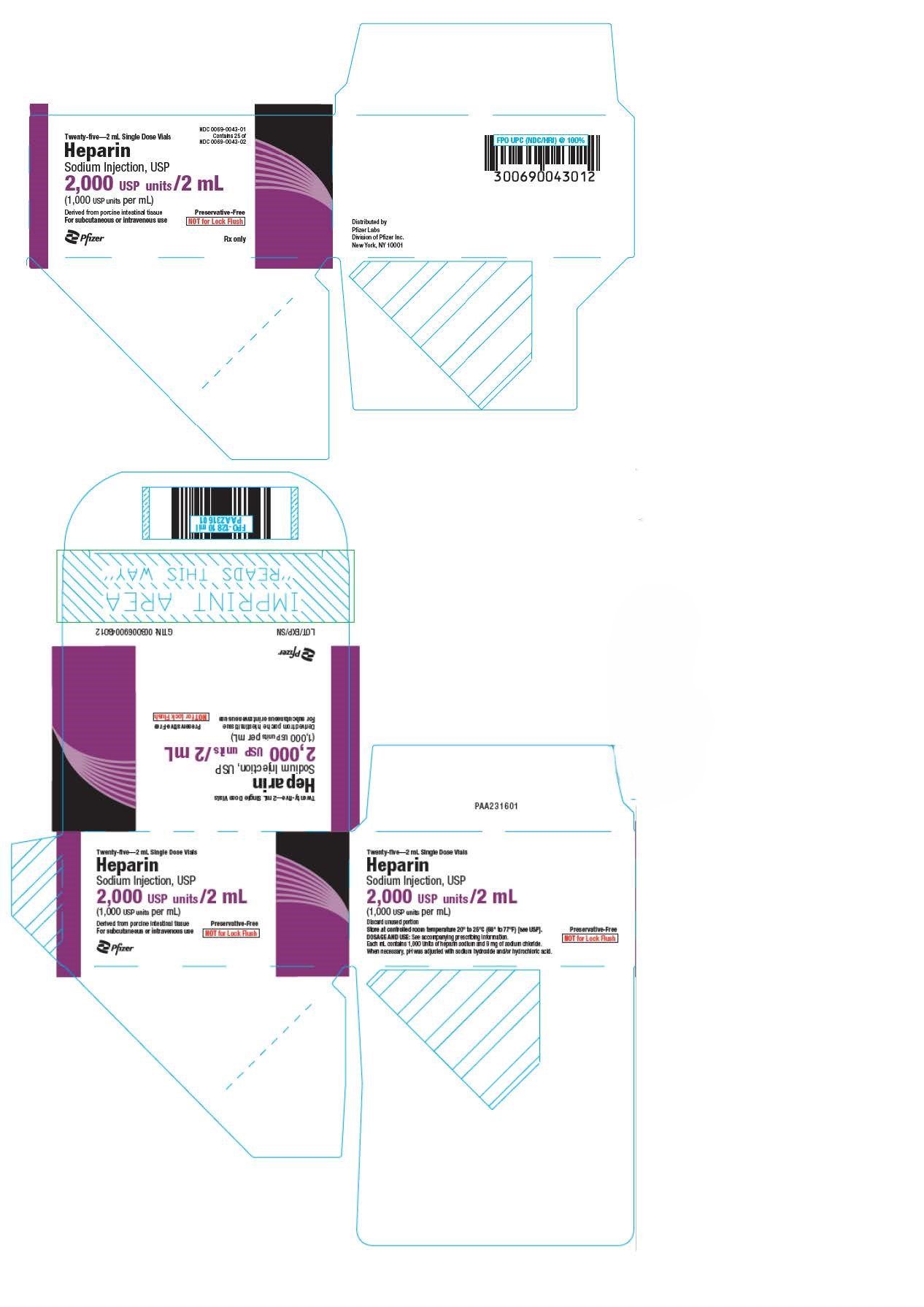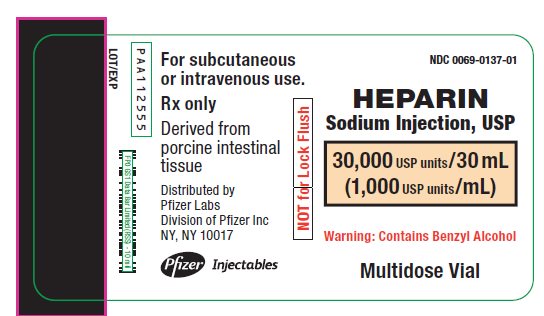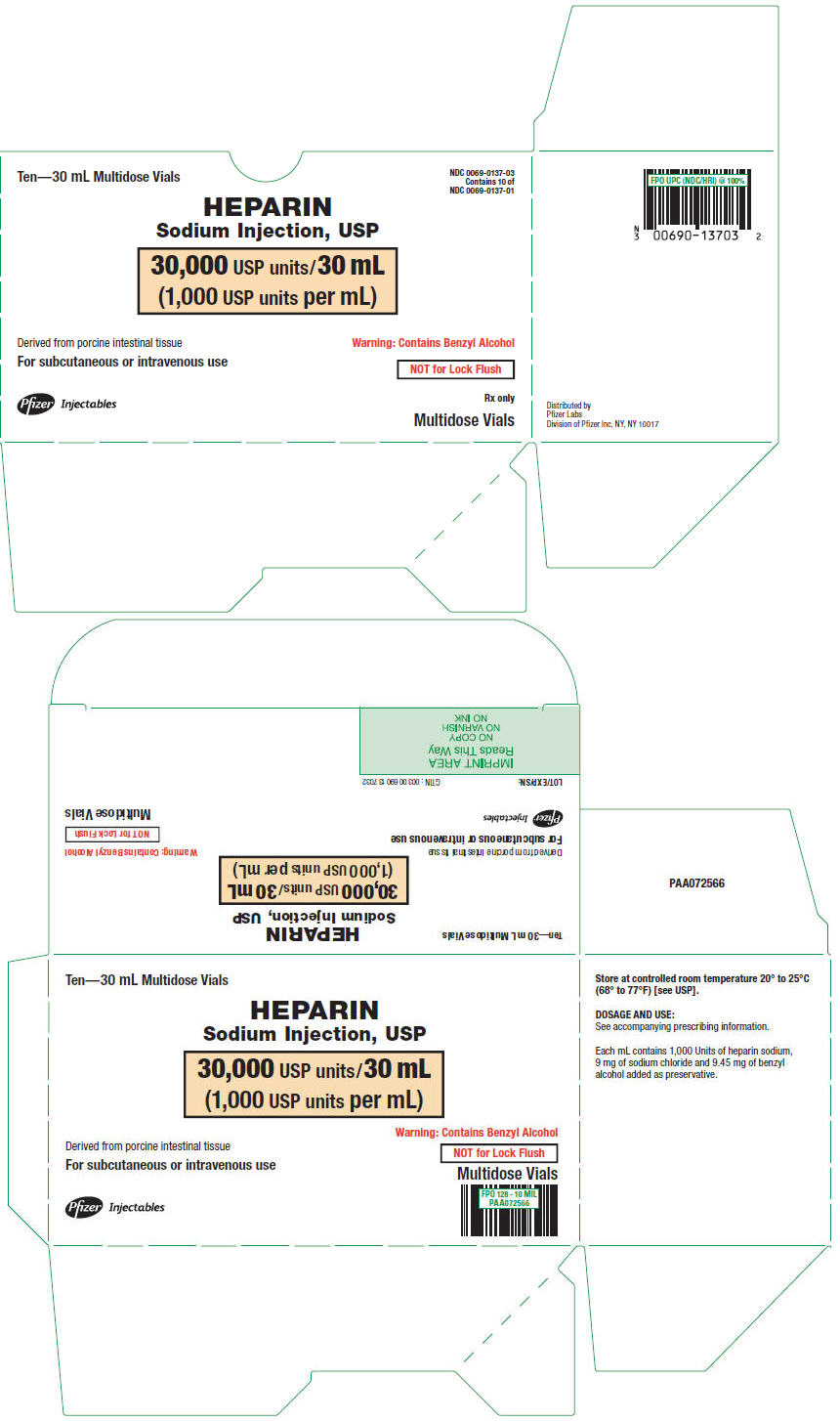 DRUG LABEL: Heparin Sodium
NDC: 0069-0058 | Form: INJECTION
Manufacturer: Pfizer Laboratories Div Pfizer Inc
Category: prescription | Type: HUMAN PRESCRIPTION DRUG LABEL
Date: 20251003

ACTIVE INGREDIENTS: HEPARIN SODIUM 1000 [USP'U]/1 mL
INACTIVE INGREDIENTS: SODIUM CHLORIDE 9 mg/1 mL; BENZYL ALCOHOL 9.45 mg/1 mL; HYDROCHLORIC ACID; SODIUM HYDROXIDE; WATER

HIGHLIGHTS OF PRESCRIBING INFORMATION

These highlights do not include all the information needed to use HEPARIN SODIUM INJECTION safely and effectively. See full prescribing information for HEPARIN SODIUM INJECTION.
HEPARIN SODIUM INJECTION, for intravenous or subcutaneous use
Initial U.S. Approval: 1939

RECENT MAJOR CHANGES

Warnings and Precautions, Unresponsiveness to Heparin with Concomitant Use with Andexanet Alfa (5.5) | 9/2025

1 INDICATIONS AND USAGE

HEPARIN SODIUM INJECTION is an anticoagulant indicated for (1):

- Prophylaxis and treatment of venous thrombosis and pulmonary embolism
- Prophylaxis and treatment of the thromboembolic complications associated with atrial fibrillation
- Treatment of acute and chronic consumption coagulopathies
- Prevention of clotting in arterial and cardiac surgery
- Prophylaxis and treatment of peripheral arterial embolism
- Anticoagulant use in transfusion, extracorporeal circulation, and dialysis procedures

2 DOSAGE AND ADMINISTRATION

Recommended Adult Dosages:

- Therapeutic Anticoagulant Effect with Full-Dose Heparin* (2.3)

Deep Subcutaneous (Intrafat) Injection Use a different site for each injection | Initial Dose | 333 units/kg subcutaneously
Deep Subcutaneous (Intrafat) Injection Use a different site for each injection | Every 12 hours | 250 units/kg subcutaneously
Intermittent Intravenous Injection | Initial Dose | 10,000 units
Intermittent Intravenous Injection | Every 4 to 6 hours | 5,000 units to 10,000 units
Continuous Intravenous Infusion | Initial Dose | 5,000 units
Continuous Intravenous Infusion | Continuous | 20,000 units/24 hours to 40,000 units/24 hours

* Based on 68 kg patient. Adjust dose based on laboratory monitoring.

- Cardiovascular Surgery (2.5)

Intravascular via Total Body Perfusion | Initial Dose | not less than 150 units/kg; adjust for longer procedures

- Low-dose Prophylaxis of Postoperative Thromboembolism (2.6)

Deep Subcutaneous (Intrafat) Injection | Initial Dose | 5,000 units 2 hours before surgery
Deep Subcutaneous (Intrafat) Injection | Every 8 to 12 hours | 5,000 units

- Extracorporeal dialysis (2.9)

Intravascular via Extracorporeal Dialysis | 25 units/kg to 30 units/kg followed by infusion rate of 1,500 units/hour to 2,000 units/hour if manufacturers' recommendations are not available

3 DOSAGE FORMS AND STRENGTHS

Preservative-free, single-dose | Preserved with Benzyl Alcohol, multiple-dose
1,000 USP units/mL Vial: 2,000 USP units/2 mL | 1,000 USP units/mL Vial: 10,000 USP units/10 mL Vial: 30,000 USP units/30 mL
 | 5,000 USP units/mL Vial: 50,000 USP units/10 mL Vial: 5,000 USP units/1 mL
 | 10,000 USP units/mL Vial: 10,000 USP units/1 mL

4 CONTRAINDICATIONS

- History of heparin-induced thrombocytopenia (HIT) or heparin-induced thrombocytopenia and thrombosis (HITTS) (4)
- History of thrombocytopenia with pentosan polysulfate (4)
- Known hypersensitivity to heparin or pork products (4)
- In whom suitable blood coagulation tests cannot be performed at appropriate intervals (4)
- An uncontrollable bleeding state, except when this is due to disseminated intravascular coagulation (4)

5 WARNINGS AND PRECAUTIONS

- Fatal Medication Errors: Confirm choice of correct strength prior to administration (5.1)
- Hemorrhage: Hemorrhage, including fatal events, has occurred in patients receiving heparin. Use caution in conditions with increased risk of hemorrhage (5.2)
- HIT and HITTS: Monitor for signs and symptoms and discontinue if indicative of HIT and HITTS (5.3)
- Benzyl Alcohol Toxicity: Use preservative-free formulation in neonates and infants (5.4)
- Monitoring: Blood coagulation tests guide therapy for full-dose heparin. Periodically monitor platelet count, hematocrit, and occult blood in stool in all patients receiving heparin (5.6, 5.7)
- Hyperkalemia: Measure blood potassium in patients at risk of hyperkalemia before starting heparin therapy and periodically in all patients (5.10)

6 ADVERSE REACTIONS

Most common adverse reactions are hemorrhage, thrombocytopenia, HIT and HITTS, injection site irritation, general hypersensitivity reactions, and elevations of aminotransferase levels. (6.1)
To report SUSPECTED ADVERSE REACTIONS, contact Pfizer at 1-800-438-1985 or FDA at 1-800-FDA-1088 or www.fda.gov/medwatch.

7 DRUG INTERACTIONS

- Drugs that interfere with coagulation, platelet aggregation or drugs that counteract coagulation may induce bleeding (7.2)
- Andexanet alfa may reduce the efficacy of heparin when used concomitantly (7.3)

8 USE IN SPECIFIC POPULATIONS

- Pregnancy: Preservative-free formulation recommended (8.1)
- Lactation: Preservative-free formulation recommended (8.2)
- Pediatric Use: Use preservative-free formulation in neonates and infants (8.4)

FULL PRESCRIBING INFORMATION

1 INDICATIONS AND USAGE

HEPARIN SODIUM INJECTION is indicated for:

- Prophylaxis and treatment of venous thrombosis and pulmonary embolism;
- Prophylaxis and treatment of thromboembolic complications associated with atrial fibrillation;
- Treatment of acute and chronic consumption coagulopathies (disseminated intravascular coagulation);
- Prevention of clotting in arterial and cardiac surgery;
- Prophylaxis and treatment of peripheral arterial embolism;
- Anticoagulant use in blood transfusions, extracorporeal circulation, and dialysis procedures.

2 DOSAGE AND ADMINISTRATION

2.1 Preparation for Administration

Confirm the choice of the correct HEPARIN SODIUM INJECTION vial to ensure that the 1 mL vial is not confused with a "catheter lock flush" vial or other 1 mL vial of incorrect strength [see Warnings and Precautions (5.1)]. Confirm the selection of the correct formulation and strength prior to administration of the drug.

Inspect parenteral drug products visually for particulate matter and discoloration prior to administration, whenever solution and container permit. Use only if solution is clear and the seal is intact. Do not use if solution is discolored or contains a precipitate.

When HEPARIN SODIUM INJECTION is added to an infusion solution for continuous intravenous (IV) administration, invert the container at least six times to ensure adequate mixing and prevent pooling of the heparin in the solution. Storage of prepared infusion solution should not exceed 4 hours at room temperature or 24 hours at 2° to 8°C (36° to 46°F). HEPARIN SODIUM INJECTION is incompatible with certain substances in solution (e.g., alteplase, amikacin sulfate, atracurium besylate, ciprofloxacin, cytarabine, daunorubicin, droperidol, erythromycin lactobionate, gentamicin sulfate, idarubicin, kanamycin sulfate, mitoxantrone HCl, polymyxin B sulfate, promethazine HCl, streptomycin sulfate, tobramycin sulfate). Consult specialized references to verify with which substances incompatibilities have been noted, as compatibility may depend on concentration, temperature, time, and other variables.

Administer HEPARIN SODIUM INJECTION by intermittent intravenous injection, intravenous infusion, or deep subcutaneous (intrafat, i.e., above the iliac crest or abdominal fat layer) injection. HEPARIN SODIUM INJECTION is not intended for intramuscular (IM) use [see Adverse Reactions (6.1)].

2.2 Laboratory Monitoring for Efficacy and Safety

Adjust the dosage of HEPARIN SODIUM INJECTION according to the patient's coagulation test results. Dosage is considered adequate when the activated partial thromboplastin time (aPTT) is 1.5 to 2 times normal or when the whole blood clotting time is elevated approximately 2.5 to 3 times the control value. When initiating treatment with HEPARIN SODIUM INJECTION by continuous intravenous infusion, determine the coagulation status (aPTT, INR, platelet count) at baseline and continue to follow aPTT approximately every 4 hours and then at appropriate intervals thereafter. When the drug is administered intermittently by intravenous injection, perform coagulation tests before each injection during initiation of treatment and at appropriate intervals thereafter. After deep subcutaneous injections, tests for adequacy of dosage are best performed on samples drawn 4 to 6 hours after the injections.

Periodically monitor platelet counts, hematocrit, and occult blood in stool during the entire course of HEPARIN SODIUM INJECTION therapy, regardless of the route of administration.

2.3 Therapeutic Anticoagulant Effect with Full-Dose Heparin

The dosing recommendations in Table 1 are based on clinical experience. Although dosages must be adjusted for the individual patient according to the results of suitable laboratory tests, the following dosage schedules may be used as guidelines:

Table 1: Recommended Adult Full-Dose Heparin Regimens for Therapeutic Anticoagulant Effect
METHOD OF ADMINISTRATION | FREQUENCY | RECOMMENDED DOSE [Based on 68 kg patient]
Deep Subcutaneous (Intrafat) Injection Use a different site for each injection to prevent the development of hematoma | Initial Dose | 333 units/kg subcutaneously
Deep Subcutaneous (Intrafat) Injection Use a different site for each injection to prevent the development of hematoma | Every 12 hours | 250 units/kg subcutaneously
Intermittent Intravenous Injection | Initial Dose | 10,000 units, either undiluted or in 50 mL to 100 mL of 0.9% Sodium Chloride Injection, USP
Intermittent Intravenous Injection | Every 4 to 6 hours | 5,000 units to 10,000 units, either undiluted or in 50 mL to 100 mL of 0.9% Sodium Chloride Injection, USP
Continuous Intravenous Infusion | Initial Dose | 5,000 units by intravenous injection
Continuous Intravenous Infusion | Continuous | 20,000 units to 40,000 units per 24 hours in 1,000 mL of 0.9% Sodium Chloride Injection, USP (or in any compatible solution) for infusion

2.4 Pediatric Use

Use preservative-free HEPARIN SODIUM INJECTION in neonates and infants.

There are no adequate and well controlled studies on heparin use in pediatric patients. Pediatric dosing recommendations are based on clinical experience. In general, the following dosage schedule may be used as a guideline in pediatric patients:

Initial Dose | 75 units/kg to 100 units/kg (intravenous bolus over 10 minutes)
Maintenance Dose | Infants: 25 units/kg/hour to 30 units/kg/hour; Infants less than 2 months have the highest requirements (average 28 units/kg/hour)
 | Children greater than 1 year of age: 18 units/kg/hour to 20 units/kg/hour; Older children may require less heparin, similar to weight-adjusted adult dosage
Monitoring | Adjust heparin to maintain aPTT of 60 seconds to 85 seconds, assuming this reflects an anti-Factor Xa level of 0.35 to 0.70.

2.5 Cardiovascular Surgery

Patients undergoing total body perfusion for open-heart surgery should receive an initial dose of not less than 150 units of heparin sodium per kilogram of body weight. Frequently, a dose of 300 units per kilogram is used for procedures estimated to last less than 60 minutes or 400 units per kilogram for those estimated to last longer than 60 minutes.

2.6 Low-Dose Prophylaxis of Postoperative Thromboembolism

The most widely used dosage has been 5,000 units 2 hours before surgery and 5,000 units every 8 to 12 hours thereafter for 7 days or until the patient is fully ambulatory, whichever is longer. Administer the heparin by deep subcutaneous (intrafat, i.e., above the iliac crest or abdominal fat layer, arm, or thigh) injection with a fine (25 to 26-gauge) needle to minimize tissue trauma.

2.7 Converting to Warfarin

To ensure continuous anticoagulation when converting from HEPARIN SODIUM INJECTION to warfarin, continue full heparin therapy for several days until the INR (prothrombin time) has reached a stable therapeutic range. Heparin therapy may then be discontinued without tapering [see Drug Interactions (7.1)].

2.8 Converting to Oral Anticoagulants other than Warfarin

For patients currently receiving intravenous heparin, stop intravenous infusion of heparin sodium immediately after administering the first dose of oral anticoagulant; or for intermittent intravenous administration of heparin sodium, start oral anticoagulant 0 to 2 hours before the time that the next dose of heparin was to have been administered.

2.9 Extracorporeal Dialysis

Follow equipment manufacturers' operating directions carefully. A dose of 25 units/kg to 30 units/kg followed by an infusion rate of 1,500 units/hour to 2,000 units/hour is suggested based on pharmacodynamic data if specific manufacturers' recommendations are not available.

3 DOSAGE FORMS AND STRENGTHS

HEPARIN SODIUM INJECTION is available as:

- 1,000 USP units/mL preservative-free, single-dose
  Vial: 2,000 USP units/2 mL
- 1,000 USP units/mL preserved with benzyl alcohol, multiple-dose
  Vial: 10,000 USP units/10 mL
  Vial: 30,000 USP units/30 mL
- 5,000 USP units/mL preserved with benzyl alcohol, multiple-dose
  Vial: 50,000 USP units/10 mL
  Vial: 5,000 USP units/1 mL
- 10,000 USP units/mL preserved with benzyl alcohol, multiple-dose
  Vial: 10,000 USP units/1 mL

4 CONTRAINDICATIONS

The use of HEPARIN SODIUM INJECTION is contraindicated in patients:

- History of heparin-induced thrombocytopenia and heparin-induced thrombocytopenia and thrombosis
- History of thrombocytopenia with pentosan polysulfate
- Known hypersensitivity to heparin or pork products (e.g., anaphylactoid reactions) [see Adverse Reactions (6.1)]
- In whom suitable blood coagulation tests (e.g., whole-blood clotting time, partial thromboplastin time) cannot be performed at appropriate intervals. This contraindication refers to full-dose heparin regimens only; there is usually no need to monitor coagulation parameters in patients receiving low-dose heparin
- An uncontrollable bleeding state [see Warnings and Precautions (5.2)], except when this is due to disseminated intravascular coagulation

5 WARNINGS AND PRECAUTIONS

5.1 Fatal Medication Errors

Do not use HEPARIN SODIUM INJECTION as a "catheter lock flush" product. HEPARIN SODIUM INJECTION is supplied in vials containing various strengths of heparin, including vials that contain a highly concentrated solution of 10,000 units in 1 mL. Fatal hemorrhages have occurred due to medication errors. Carefully examine all HEPARIN SODIUM INJECTION vials to confirm the correct vial choice prior to administration of the drug.

5.2 Hemorrhage

Avoid using heparin in the presence of major bleeding, except when the benefits of heparin therapy outweigh the potential risks.

Hemorrhage, including fatal events, has occurred in patients receiving heparin. Hemorrhage can occur at virtually any site in patients receiving heparin. Adrenal hemorrhage (with resultant acute adrenal insufficiency), ovarian hemorrhage, and retroperitoneal hemorrhage have occurred during anticoagulant therapy with heparin [see Adverse Reactions (6.1]). A higher incidence of bleeding has been reported in patients, particularly women, over 60 years of age [see Clinical Pharmacology (12.3)]. An unexplained fall in hematocrit or fall in blood pressure should lead to serious consideration of a hemorrhagic event.

Use heparin sodium with caution in disease states in which there is increased risk of hemorrhage, including:

- Cardiovascular – Subacute bacterial endocarditis, severe hypertension.
- Surgical – During and immediately following: (a) spinal puncture or spinal anesthesia or (b) major surgery, especially involving the brain, spinal cord, or eye.
- Hematologic – Conditions associated with increased bleeding tendencies, such as hemophilia, thrombocytopenia, and some vascular purpuras.
- Patients with hereditary antithrombin III deficiency receiving concurrent antithrombin III therapy – The anticoagulant effect of heparin is enhanced by concurrent treatment with antithrombin III (human) in patients with hereditary antithrombin III deficiency. To reduce the risk of bleeding, reduce the heparin dose during concomitant treatment with antithrombin III (human).
- Gastrointestinal – Ulcerative lesions, continuous tube drainage of the stomach or small intestine, and clinical settings in which stress-induced gastrointestinal hemorrhage is possible.
- Other – Menstruation, liver disease with impaired hemostasis, severe renal disease, or in patients with indwelling catheters.

5.3 Heparin-Induced Thrombocytopenia and Heparin-Induced Thrombocytopenia and Thrombosis

Heparin-induced thrombocytopenia (HIT) is a serious antibody-mediated reaction resulting from irreversible aggregation of platelets. HIT occurs in patients treated with heparin and is due to the development of antibodies to a platelet Factor 4-heparin complex that induce in vivo platelet aggregation. HIT may progress to the development of venous and arterial thromboses, a condition known as heparin-induced thrombocytopenia and thrombosis (HITT). Thrombotic events may also be the initial presentation for HITT. These serious thromboembolic events include deep vein thrombosis, pulmonary embolism, cerebral vein thrombosis, limb ischemia, stroke, myocardial infarction, mesenteric thrombosis, renal arterial thrombosis, skin necrosis, gangrene of the extremities that may lead to amputation, and possibly death. Monitor thrombocytopenia of any degree closely. If the platelet count falls below 100,000/mm^3 or if recurrent thrombosis develops, promptly discontinue heparin, evaluate for HIT and HITT, and, if necessary, administer an alternative anticoagulant. HIT and HITT can occur up to several weeks after the discontinuation of heparin therapy. Patients presenting with thrombocytopenia or thrombosis after discontinuation of heparin should be evaluated for HIT and HITT.

5.4 Risk of Serious Adverse Reactions in Infants due to Benzyl Alcohol Preservative

Use preservative-free HEPARIN SODIUM INJECTION in neonates and infants.

Serious and fatal adverse reactions including "gasping syndrome" can occur in neonates and low-birth weight infants treated with benzyl alcohol-preserved formulation in infusion solutions, including HEPARIN SODIUM INJECTION. The "gasping syndrome" is characterized by central nervous system depression, metabolic acidosis, and gasping respirations.

When prescribing HEPARIN SODIUM INJECTION in infants consider the combined daily metabolic load of benzyl alcohol from all sources including HEPARIN SODIUM INJECTION (HEPARIN SODIUM INJECTION contains 9.45 mg of benzyl alcohol per mL) and other drugs containing benzyl alcohol. The minimum amount of benzyl alcohol at which toxicity may occur is not known [see Use in Specific Populations (8.4)].

5.5 Unresponsiveness to Heparin with Concomitant Use with Andexanet Alfa

Unresponsiveness to unfractionated heparin leading to non-prolongation of activated clotting times and serious thrombotic events has occurred when unfractionated heparin was administered after use of andexanet alfa for the reversal of direct Factor Xa inhibitors (apixaban and rivaroxaban). Avoid use of heparin after use of andexanet alfa. Use an alternative anticoagulant to heparin [see Drug Interactions (7.3)].

5.6 Thrombocytopenia

Thrombocytopenia in patients receiving heparin has been reported at frequencies up to 30%. It can occur 2 to 20 days (average 5 to 9) following the onset of heparin therapy. Obtain platelet counts before and periodically during heparin therapy. Monitor thrombocytopenia of any degree closely. If the count falls below 100,000/mm^3 or if recurrent thrombosis develops, promptly discontinue heparin, evaluate for HIT and HITT, and, if necessary, administer an alternative anticoagulant [see Warnings and Precautions (5.3)].

5.7 Coagulation Testing and Monitoring

When using a full dose heparin regimen, adjust the heparin dose based on frequent blood coagulation tests. If the coagulation test is unduly prolonged or if hemorrhage occurs, discontinue heparin promptly [see Overdosage (10)]. Periodically monitor platelet counts, hematocrit, and occult blood in stool during the entire course of heparin therapy, regardless of the route of administration [see Dosage and Administration (2.2)].

5.8 Heparin Resistance

Resistance to heparin is frequently encountered in fever, thrombosis, thrombophlebitis, infections with thrombosing tendencies, myocardial infarction, cancer, in postsurgical patients, and patients with antithrombin III deficiency. Close monitoring of coagulation tests is recommended in these cases. Adjustment of heparin doses based on anti-Factor Xa levels may be warranted.

5.9 Hypersensitivity

Patients with documented hypersensitivity to heparin should be given the drug only in clearly life-threatening situations.

Because HEPARIN SODIUM INJECTION is derived from animal tissue, it should be used with caution in patients with a history of allergy.

5.10 Hyperkalemia

Heparin can suppress adrenal secretion of aldosterone leading to hyperkalemia, particularly in patients with diabetes mellitus, chronic renal failure, pre-existing metabolic acidosis, a raised plasma potassium, or taking potassium sparing drugs. The risk of hyperkalemia appears to increase with duration of therapy but is usually reversible upon discontinuation of heparin.

Measure blood potassium in patients at risk of hyperkalemia before starting heparin therapy and periodically in all patients treated for more than 5 days or earlier as deemed fit by the clinician.

6 ADVERSE REACTIONS

The following clinically significant adverse reactions are described elsewhere in the labeling:

- Hemorrhage [see Warnings and Precautions (5.2)]
- Heparin-Induced Thrombocytopenia and Heparin-Induced Thrombocytopenia and Thrombosis [see Warnings and Precautions (5.3)]
- Risk of Serious Adverse Reactions in Infants due to Benzyl Alcohol Preservative [see Warnings and Precautions (5.4)]
- Thrombocytopenia [see Warnings and Precautions (5.6)]
- Heparin Resistance [see Warnings and Precautions (5.8)]
- Hypersensitivity [see Warnings and Precautions (5.9)]
- Hyperkalemia [see Warnings and Precautions (5.10)]

6.1 Postmarketing Experience

The following adverse reactions have been identified during post approval use of HEPARIN SODIUM INJECTION. Because these reactions are reported voluntarily from a population of uncertain size, it is not always possible to reliably estimate their frequency.

- Hemorrhage – Hemorrhage is the chief complication that may result from heparin therapy [see Warnings and Precautions (5.2)]. Gastrointestinal or urinary tract bleeding during anticoagulant therapy may indicate the presence of an underlying occult lesion. Bleeding can occur at any site but certain specific hemorrhagic complications may be difficult to detect including:
  - Adrenal hemorrhage, with resultant acute adrenal insufficiency, has occurred with heparin therapy, including fatal cases.
  - Ovarian (corpus luteum) hemorrhage developed in a number of women of reproductive age receiving short- or long-term heparin therapy.
  - Retroperitoneal hemorrhage.
- HIT and HITT, including delayed onset cases [see Warnings and Precautions (5.3)].
- Local irritation – Local irritation, erythema, mild pain, hematoma, or ulceration have occurred following deep subcutaneous (intrafat) injection of heparin sodium. Because such reactions occur more frequently after intramuscular administration, the IM route is not recommended.
- Histamine-like reactions – Such reactions have been observed at the site of injection. Necrosis of the skin has been reported at the site of subcutaneous injection of heparin, occasionally requiring skin grafting [see Warnings and Precautions (5.3)].
- Hypersensitivity – Generalized hypersensitivity reactions have been reported with chills, fever, and urticaria as the most usual manifestations; asthma, rhinitis, lacrimation, headache, nausea and vomiting, and anaphylactoid reactions, including shock, occur less frequently. Itching and burning, especially on the plantar site of the feet, may occur.
- Metabolism and Nutrition Disorders – Hyperkalemia.
- Elevations of serum aminotransferases – Significant elevations of aspartate aminotransferase (AST) and alanine aminotransferase (ALT) levels have occurred in patients who have received heparin.
- Others – Osteoporosis following long-term administration of high doses of heparin, cutaneous necrosis after systemic administration, suppression of aldosterone synthesis, delayed transient alopecia, priapism, and rebound hyperlipemia on discontinuation of heparin sodium have been reported.

7 DRUG INTERACTIONS

7.1 Oral Anticoagulants

Heparin sodium may prolong the one-stage prothrombin time. Therefore, when heparin sodium is given with dicumarol or warfarin sodium, a period of at least 5 hours after the last intravenous dose or 24 hours after the last subcutaneous dose should elapse before blood is drawn if a valid prothrombin time is to be obtained.

7.2 Platelet Inhibitors

Drugs such as NSAIDs (including salicylic acid, ibuprofen, indomethacin, and celecoxib), dextran, phenylbutazone, thienopyridines, dipyridamole, hydroxychloroquine, glycoprotein IIb/IIIa antagonists (including abciximab, eptifibatide, and tirofiban), and others that interfere with platelet-aggregation reactions (the main hemostatic defense of heparinized patients) may induce bleeding and should be used with caution in patients receiving heparin sodium.

7.3 Unresponsiveness to Heparin with Concomitant Use with Andexanet Alfa

Andexanet binds to heparin-bound antithrombin III (ATIII) and may reduce the anticoagulant effect of heparin. Unresponsiveness to unfractionated heparin may lead to serious and life-threatening thrombotic events. Use of andexanet alfa as an antidote for heparin has not been established. Avoid use of heparin after use of andexanet alfa for the reversal of direct Factor Xa inhibitors (apixaban and rivaroxaban). If anticoagulation is needed, use an alternative anticoagulant to heparin [see Warnings and Precautions (5.5)].

7.4 Other Interactions

Digitalis, tetracyclines, nicotine, or antihistamines, or intravenous (IV) nitroglycerin may partially counteract the anticoagulant action of heparin sodium.

Antithrombin III (human) – The anticoagulant effect of heparin is enhanced by concurrent treatment with antithrombin III (human) in patients with hereditary antithrombin III deficiency. To reduce the risk of bleeding, a reduced dosage of heparin is recommended during treatment with antithrombin III (human).

8 USE IN SPECIFIC POPULATIONS

8.1 Pregnancy

Risk Summary

There are no available data on heparin sodium use in pregnant women to infor a drug associated risk of major birth defects and miscarriage. In published reports, heparin exposure during pregnancy did not show evidence of an increased risk of adverse maternal or fetal outcomes in humans. No teratogenicity, but early embryo-fetal death was observed in animal reproductive studies with administration of heparin sodium to pregnant rats and rabbits during organogenesis at doses approximately 10 times the maximum recommended human dose (MRHD) of 40,000 USP units/24 hours infusion (see Data). Consider the benefits and risks of HEPARIN SODIUM INJECTION to a pregnant woman and possible risks to the fetus when prescribing HEPARIN SODIUM INJECTION to a pregnant woman.

If available, preservative-free HEPARIN SODIUM INJECTION is recommended when heparin therapy is needed during pregnancy. There are no known adverse outcomes associated with fetal exposure to the preservative benzyl alcohol through maternal drug administration; however, the preservative benzyl alcohol can cause serious adverse events and death when administered intravenously to neonates and infants [see Use in Specific Populations (8.4)].

The estimated background risk of major birth defects and miscarriage for the indicated population is unknown. All pregnancies have a risk of birth defect, loss, or other adverse outcomes. In the U.S. general population, the estimated background risk of major birth defects and miscarriage in clinically recognized pregnancies is 2–4% and 15–20%, respectively.

Data

Human Data

The maternal and fetal outcomes associated with uses of heparin via various dosing methods and administration routes during pregnancy have been investigated in numerous studies. These studies generally reported normal deliveries with no maternal or fetal bleeding and no other complications.

Animal Data

In a published study conducted in rats and rabbits, pregnant animals received heparin intravenously during organogenesis at a dose of 10,000 units/kg/day, approximately 10 times the maximum human daily dose based on body weight. The number of early resorptions increased in both species. There was no evidence of teratogenic effects.

8.2 Lactation

Risk Summary

There is no information regarding the presence of heparin in human milk, the effects on the breastfed child, or the effects on milk production. Due to its large molecular weight, heparin is not likely to be excreted in human milk, and any heparin in milk would not be orally absorbed by a breastfed child. The developmental and health benefits of breastfeeding should be considered along with the mother's clinical need for HEPARIN SODIUM INJECTION and any potential adverse effects on the breastfed child from HEPARIN SODIUM INJECTION or from the underlying maternal condition. Benzyl alcohol present in maternal serum is likely to cross into human milk and may be orally absorbed by a nursing infant [see Use in Specific Populations (8.4)].

8.4 Pediatric Use

There are no adequate and well controlled studies on heparin use in pediatric patients. Pediatric dosing recommendations are based on clinical experience [see Dosage and Administration (2.4)].

Carefully examine all HEPARIN SODIUM INJECTION vials to confirm choice of the correct strength prior to administration of the drug. Pediatric patients, including neonates, have died as a result of medication errors [see Warnings and Precautions (5.1)].

Benzyl Alcohol Toxicity

Use preservative-free HEPARIN SODIUM INJECTION in neonates and infants.

Serious adverse reactions including fatal reactions and the "gasping syndrome" occurred in premature neonates and low-birth weight infants in the neonatal intensive care unit who received benzyl alcohol as a preservative in infusion solutions. In these cases, benzyl alcohol dosages of 99 to 234 mg/kg/day produced high levels of benzyl alcohol and its metabolites in the blood and urine (blood levels of benzyl alcohol were 0.61 to 1.378 mmol/L). Additional adverse reactions included gradual neurological deterioration, seizures, intracranial hemorrhage, hematologic abnormalities, skin breakdown, hepatic and renal failure, hypotension, bradycardia, and cardiovascular collapse. Preterm, low-birth weight infants may be more likely to develop these reactions because they may be less able to metabolize benzyl alcohol.

When prescribing HEPARIN SODIUM INJECTION in infants consider the combined daily metabolic load of benzyl alcohol from all sources including HEPARIN SODIUM INJECTION (HEPARIN SODIUM INJECTION contains 9.45 mg of benzyl alcohol) and other drugs containing benzyl alcohol. The minimum amount of benzyl alcohol at which serious adverse reactions may occur is not known [see Warnings and Precautions (5.4)].

8.5 Geriatric Use

There are limited adequate and well-controlled studies in patients 65 years and older, however a higher incidence of bleeding has been reported in patients over 60 years of age, especially women [see Warnings and Precautions (5.2)]. Lower doses of heparin may be indicated in these patients [see Clinical Pharmacology (12.3)].

10 OVERDOSAGE

Bleeding is the chief sign of heparin overdosage.

Neutralization of Heparin Effect

When clinical circumstances (bleeding) require reversal of the heparin effect, protamine sulfate (1% solution) by slow infusion will neutralize heparin sodium. No more than 50 mg should be administered, very slowly, in any 10 minute period. Each mg of protamine sulfate neutralizes approximately 100 USP heparin units. The amount of protamine required decreases over time as heparin is metabolized. Although the metabolism of heparin is complex, it may, for the purpose of choosing a protamine dose, be assumed to have a half-life of about 30 minutes after intravenous injection. Because fatal reactions often resembling anaphylaxis have been reported with protamine, it should be given only when resuscitation techniques and treatment of anaphylactoid shock are readily available. For additional information, consult the prescribing information for protamine sulfate injection.

Consider contacting the Poison Help line (1-800-222-1222) or a medical toxicologist for additional overdose management recommendations.

11 DESCRIPTION

Heparin is a heterogenous group of straight-chain anionic mucopolysaccharides, called glycosaminoglycans, possessing anticoagulant properties. It is composed of polymers of alternating derivations of α-D-glucosamido (N-sulfated O-sulfated or N-acetylated) and O-sulfated uronic acid (α-L-iduronic acid or β-D-glucuronic acid).

Structure of heparin sodium (representative subunits):

HEPARIN SODIUM INJECTION is a sterile preparation of heparin sodium derived from porcine intestinal tissue, standardized for anticoagulant activity, in water for injection. It is intended for intravenous or deep subcutaneous administration. The potency is determined by a biological assay using a USP reference standard based on units of heparin activity per milligram.

For formulations preserved with benzyl alcohol, each mL of the 1,000 UPS units and 5,000 USP units per mL preparations contains: heparin sodium 1,000 UPS units or 5,000 USP units; 9 mg sodium chloride; 9.45 mg benzyl alcohol added as preservative. Each mL of the 10,000 USP units per mL preparations contains: heparin sodium 10,000 USP units; 9.45 mg benzyl alcohol added as preservative.

The preservative-free product contains (per mL): 1,000 USP units of heparin sodium and 9 mg sodium chloride.

When necessary, the pH of HEPARIN SODIUM INJECTION is adjusted with hydrochloric acid and/or sodium hydroxide. The pH range is 5.0 to 7.5.

12 CLINICAL PHARMACOLOGY

12.1 Mechanism of Action

Heparin interacts with the naturally occurring plasma protein, Antithrombin III, to induce a conformational change, which markedly enhances the serine protease activity of Antithrombin III, thereby inhibiting the activated coagulation factors involved in the clotting sequence, particularly Xa and IIa. Small amounts of heparin inhibit Factor Xa, and larger amounts inhibit thrombin (Factor IIa). Heparin also prevents the formation of a stable fibrin clot by inhibiting the activation of the fibrin stabilizing factor. Heparin does not have fibrinolytic activity; therefore, it will not lyse existing clots.

12.2 Pharmacodynamics

Various times (activated clotting time, activated partial thromboplastin time, prothrombin time, whole blood clotting time) are prolonged by full therapeutic doses of heparin; in most cases, they are not measurably affected by low doses of heparin. The bleeding time is usually unaffected by heparin.

12.3 Pharmacokinetics

Absorption

Heparin is not absorbed through the gastrointestinal tract and therefore administered via parenteral route. Peak plasma concentration and the onset of action are achieved immediately after intravenous administration.

Distribution

Heparin is highly bound to antithrombin, fibrinogens, globulins, serum proteases and lipoproteins. The volume of distribution is 0.07 L/kg.

Elimination

Metabolism

Heparin does not undergo enzymatic degradation.

Excretion

Heparin is mainly cleared from the circulation by liver and reticuloendothelial cells mediated uptake into extravascular space. Heparin undergoes biphasic clearance, a) rapid saturable clearance (zero order process due to binding to proteins, endothelial cells and macrophage) and b) slower first order elimination. The plasma half-life is dose-dependent and it ranges from 0.5 to 2 h.

Specific Populations

Geriatric patients

Patients over 60 years of age, following similar doses of heparin, may have higher plasma levels of heparin and longer activated partial thromboplastin times (aPTTs) compared with patients under 60 years of age [see Use in Specific Populations (8.5)].

13 NONCLINICAL TOXICOLOGY

13.1 Carcinogenesis, Mutagenesis, Impairment of Fertility

No long-term studies in animals have been performed to evaluate carcinogenic potential of heparin. No studies in animals have been performed addressing mutagenesis or impairment of fertility.

16 HOW SUPPLIED/STORAGE AND HANDLING

HEPARIN SODIUM INJECTION preservative-free is available in the following strengths and package sizes:

DESCRIPTION | NDC
1,000 USP units/mL
Preservative-free, 25 vials: 2,000 USP units/2 mL, single-dose [Discard unused portion] | 0069-0043-01

HEPARIN SODIUM INJECTION preserved with benzyl alcohol is available in the following strengths and package sizes:

DESCRIPTION | NDC
1,000 USP units/mL
25 vials: 10,000 USP units/10 mL, multiple-dose | 0069-0058-01
10 vials: 30,000 USP units/30 mL, multiple-dose | 0069-0137-03
5,000 USP units/mL
25 vials: 50,000 USP units/10 mL, multiple-dose | 0069-0059-01
25 vials: 5,000 USP units/1 mL, multiple-dose | 0069-0059-03
10,000 USP units/mL
25 vials: 10,000 USP units/1 mL, multiple-dose | 0069-0062-01

STORAGE AND HANDLING

Store at 20° to 25°C (68° to 77°F) [see USP Controlled Room Temperature]. Use only if solution is clear and the seal is intact. Do not use if solution is discolored or contains a precipitate.

17 PATIENT COUNSELING INFORMATION

Hemorrhage

Inform patients that it may take them longer than usual to stop bleeding, that they may bruise and/or bleed more easily when they are treated with heparin, and that they should report any unusual bleeding or bruising to their physician. Hemorrhage can occur at virtually any site in patients receiving heparin. Fatal hemorrhages have occurred [see Warnings and Precautions (5.2)].

Prior to Surgery

Advise patients to inform physicians and dentists that they are receiving heparin before any surgery is scheduled [see Warnings and Precautions (5.2)].

Heparin-Induced Thrombocytopenia

Inform patients of the risk of heparin-induced thrombocytopenia (HIT). HIT may progress to the development of venous and arterial thromboses, a condition known as heparin-induced thrombocytopenia and thrombosis (HITT). HIT and HITT can occur up to several weeks after the discontinuation of heparin therapy [see Warnings and Precautions (5.3)].

Hypersensitivity

Inform patients that generalized hypersensitivity reactions have been reported. Necrosis of the skin has been reported at the site of subcutaneous injection of heparin [see Warnings and Precautions (5.9), Adverse Reactions (6.1)].

Other Medications

Because of the risk of hemorrhage, advise patients to inform their physicians and dentists of all medications they are taking, including non-prescription medications, and before starting any new medication [see Drug Interactions (7.1)].

This product’s labeling may have been updated. For the most recent prescribing information, please visit www.pfizer.com.

For medical information about HEPARIN SODIUM INJECTION, please visit www.pfizermedinfo.com or call 1-800-438-1985.

LAB-0414-9.0

PRINCIPAL DISPLAY PANEL - 10,000 USP units/10 mL Multidose Vial Label

NDC 0069-0058-02

Multidose Vial

Heparin
Sodium Injection, USP

10,000 USP units /
10 mL
(1,000 USP units/mL)

Warning: Contains
Benzyl Alcohol

Rx only

PRINCIPAL DISPLAY PANEL - 10,000 USP units/10 mL Multidose Vial Carton

NDC 0069-0058-01
Contains 25 of NDC 0069-0058-02
Rx only

Twenty-five—10 mL Multidose Vials

Heparin
Sodium Injection, USP

10,000 USP units/10 mL
(1,000 USP units per mL)

Derived from porcine intestinal tissue

For subcutaneous or intravenous use

Warning: Contains Benzyl Alcohol

NOT for Lock Flush

Pfizer Injectables

PRINCIPAL DISPLAY PANEL - 50,000 USP units/10 mL Multidose Vial Label

NDC 0069-0059-02

Multidose Vial

Heparin
Sodium Injection, USP

50,000 USP units /
10 mL
(1,000 USP units/mL)

Warning: Contains
Benzyl Alcohol

Rx only

PRINCIPAL DISPLAY PANEL - 50,000 USP units/10 mL Multidose Vial Carton

NDC 0069-0059-01
Contains 25 of NDC 0069-0059-02
Rx only

Twenty-five—10 mL Multidose Vials

Heparin
Sodium Injection, USP

50,000 USP units/10 mL
(5,000 USP units per mL)

Derived from porcine intestinal tissue

For subcutaneous or intravenous use

Warning: Contains Benzyl Alcohol

NOT for Lock Flush

Pfizer Injectables

PRINCIPAL DISPLAY PANEL - 1 mL Multidose Vial Label

NDC 0069-0062-02

Multidose Vial

Heparin
Sodium Injection, USP

10,000 USP units / mL

Warning: Contains
Benzyl Alcohol

Rx only

PRINCIPAL DISPLAY PANEL - 1 mL Multidose Vial Carton

NDC 0069-0062-01
Contains 25 of
NDC 0069-0062-02
Rx only

Twenty-five—1 mL Multidose Vials

Heparin
Sodium Injection, USP

10,000 USP units /mL

Derived from porcine intestinal tissue

For subcutaneous or intravenous use

Warning: Contains Benzyl Alcohol

Pfizer Injectables

NOT for Lock Flush

PRINCIPAL DISPLAY PANEL - 2 mL Single Dose Vial Label

NDC 0069-0043-02

Single Dose Vial

Heparin
Sodium Injection, USP

2,000 USP units / 2 mL
(1,000 USP units/mL)

Preservative-Free
Rx only

PRINCIPAL DISPLAY PANEL - 2 mL Single Dose Vial Carton

NDC 0069-0043-01
Contains 25 of
NDC 0069-0043-02

Twenty-five—2 mL Single Dose Vials

Heparin
Sodium Injection, USP

2,000 USP units /2 mL
(1,000 USP units per mL)

Derived from porcine intestinal tissue

For subcutaneous or intravenous use

Pfizer

Preservative-Free

NOT for Lock Flush

Rx only

PRINCIPAL DISPLAY PANEL - 30 mL Multidose Vial Label

NDC 0069-0137-01

HEPARIN
Sodium Injection, USP

30,000 USP units/30 mL
(1,000 USP units/mL)

Warning: Contains Benzyl Alcohol

Multidose Vial

NOT for Lock Flush

PRINCIPAL DISPLAY PANEL - 30 mL Vial Carton

Ten—30 mL Multidose Vials

NDC 0069-0137-03
Contains 10 of
NDC 0069-0137-01

HEPARIN
Sodium Injection, USP

30,000 USP units/30 mL
(1,000 USP units per mL)

Derived from porcine intestinal tissue

For subcutaneous or intravenous use

Pfizer Injectables

Warning: Contains Benzyl Alcohol

NOT for Lock Flush

Rx only

Multidose Vials